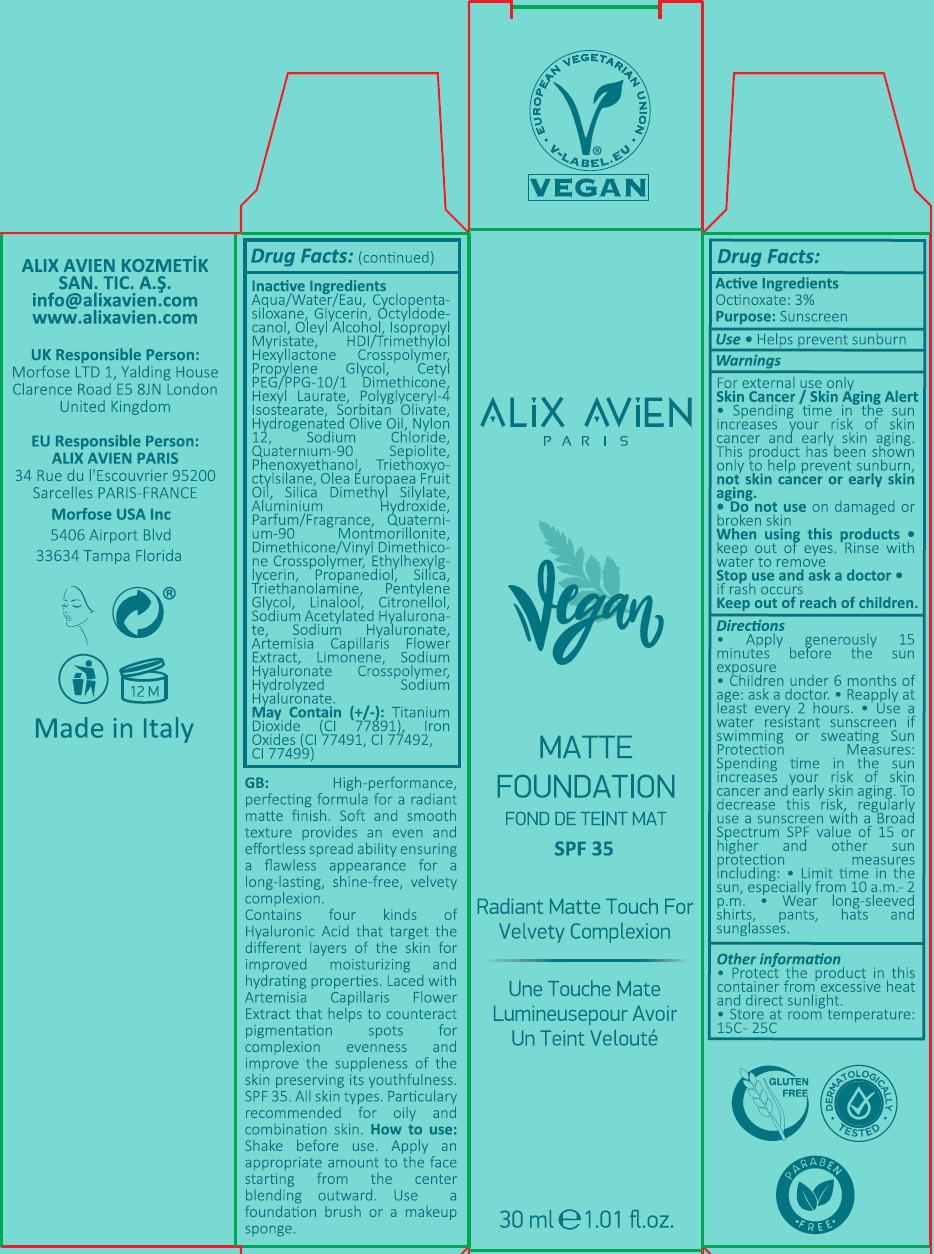 DRUG LABEL: Alix Avien
NDC: 82668-110 | Form: LIQUID
Manufacturer: ALIX AVIEN KOZMETIK SANAYI TICARET ANONIM SIRKETI
Category: otc | Type: HUMAN OTC DRUG LABEL
Date: 20220408

ACTIVE INGREDIENTS: OCTINOXATE 30 mg/1 mL
INACTIVE INGREDIENTS: WATER; CYCLOMETHICONE 5; GLYCERIN; OCTYLDODECANOL; OLEYL ALCOHOL; ISOPROPYL MYRISTATE; HEXAMETHYLENE DIISOCYANATE/TRIMETHYLOL HEXYLLACTONE CROSSPOLYMER; PROPYLENE GLYCOL; CETYL PEG/PPG-10/1 DIMETHICONE (HLB 2); HEXYL LAURATE; POLYGLYCERYL-4 ISOSTEARATE; SORBITAN OLIVATE; HYDROGENATED OLIVE OIL; NYLON-12; SODIUM CHLORIDE; QUATERNIUM-90 SEPIOLITE; PHENOXYETHANOL; TRIETHOXYCAPRYLYLSILANE; OLIVE OIL; SILICA DIMETHYL SILYLATE; ALUMINUM HYDROXIDE; QUATERNIUM-90 MONTMORILLONITE; DIMETHICONE/VINYL DIMETHICONE CROSSPOLYMER (SOFT PARTICLE); ETHYLHEXYLGLYCERIN; PROPANEDIOL; SILICON DIOXIDE; TROLAMINE; PENTYLENE GLYCOL; LINALOOL, (+/-)-; .BETA.-CITRONELLOL, (R)-; SODIUM ACETYLATED HYALURONATE; HYALURONATE SODIUM; ARTEMISIA CAPILLARIS FLOWER; LIMONENE, (+)-; TITANIUM DIOXIDE; FERRIC OXIDE RED; FERRIC OXIDE YELLOW; FERROSOFERRIC OXIDE

ALIX AVIEN Vegan MATTE FOUNDATION SPF 35

Active Ingredients

Octinoxate: 3%

Purpose:

Sunscreen

Use

• Helps prevent sunburn

Warnings

For external use only

Skin Cancer / Skin Aging Alert • Spending time in the sun increases your risk of skin cancer and early skin aging. This product has been shown only to help prevent sunburn, not skin cancer or early skin aging.

• Do not use on damaged or broken skin

When using this products • keep out of eyes. Rinse with water to remove.

Stop use and ask a doctor • if rash occurs

Keep out of reach of children.

Directions

• Apply generously 15 minutes before the sun exposure
• Children under 6 months of age: ask a doctor. • Reapply at least every 2 hours. • Use a water resistant sunscreen if swimming or sweating Sun Protection Measures: Spending time in the sun increases your risk of skin cancer and early skin aging. To decrease this risk, regularly use a sunscreen with a Broad Spectrum SPF value of 15 or higher ad other sun protection measures including: • Limit time in the sun, especially from 10 a.m. - 2 p.m. • Wear long-sleeved shirts, pants, hats and sunglasses.

Other information

• Protect the product in this container from excessive heat and direct sunlight.
• Store at room temperature: 15C - 25C

Inactive Ingredients

Aqua/Water/Eau, Cyclopentasiloxane, Glycerin, Octyldodecanol, Oleyl Alcohol, Isopropyl Myristate, HDI/Trimethylol Hexyllactone Crosspolymer, Propylene Glycol, Cetyl PEG/PPG-10/1 Dimethicone, Hexyl Laurate, Polyglyceryl-4 Isostearate, Sorbitan Olivate, Hydrogenated Olive Oil, Nylon 12, Sodium Chloride, Quaternium-90 Sepiolite, Phenoxyethanol, Triethoxyoctylsilane, Olea Europaea Fruit Oil, Silica Dimethyl Silylate, Aluminium Hydroxide, Parfum/Fragrance, Quaternium-90 Montmorillonite, Dimethicone/Vinyl Dimethicone Crosspolymer, Ethylhexylglycerin, Propanediol, Silica, Triethanolamine, Pentylene Glycol, Linalool, Citronellol, Sodium Acetylated Hyaluronate, Sodium Hyaluronate, Artemisia Capillaris Flower Extract, Limonene, Sodium Hyaluronate Crosspolymer, Hydrolyzed Sodium Hyaluronate.
May Contain (+/-): Titanium Dioxide (CI 77891), Iron Oxides (CI 77491, CI 77492, CI 77499)

Radiant Matte Touch For Velvety Complexion

GB: High-performance, perfecting formula for a radiant matte finish. Soft and smooth texture provides an even and effortless spread ability ensuring a flawless appearance for a long-lasting, shine-free, velvety complexion.
Contains four kinds of Hyaluronic Acid that target the different layers of the skin for improved moisturizing and hydrating properties. Laced with Artemisia Capillaris Flower Extract that helps to counteract pigmentation spots for complexion evenness and improve the suppleness of the skin preserving its youthfulness. SPF 35. All skin types. Particularly recommended for oily and combination skin. How to use: Shake before use. Apply an appropriate amount to the face starting from the center blending outward. Use a foundation brush or a makeup sponge.

EUROPEAN VEGETARIAN UNION • V-LABEL.EU •

GLUTEN FREE

DERMATOLOGICALLY TESTED

PARABEN FREE

ALIX AVIEN KOZMETIK SAN. TIC. A.S.
info@alixavien.com
www.alixavien.com

UK Responsible Person:
Morfose LTD 1, Yalding House
Clarence Road E5 8JN London
United Kingdom

EU Responsible Person:
ALIX AVIEN PARIS
34 Rue du l'Escouvrier 95200
Sarcelles PARIS-FRANCE

Morfose USA Inc
5406 Airport Blvd
33634 Tampa Florida

Made in Italy